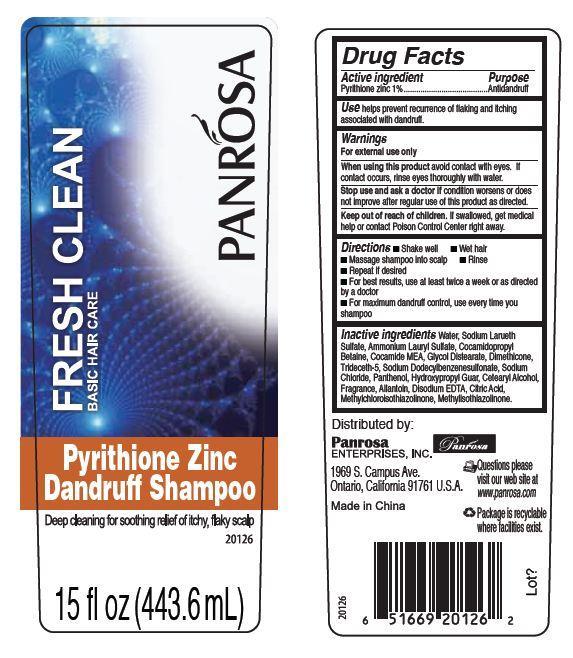 DRUG LABEL: Panrosa FRESH CLEAN Pyrithione Zinc Dandruff
NDC: 50302-400 | Form: SHAMPOO
Manufacturer: Panrosa Enterprises, Inc.
Category: otc | Type: HUMAN OTC DRUG LABEL
Date: 20211020

ACTIVE INGREDIENTS: PYRITHIONE ZINC 10 mg/1 mL
INACTIVE INGREDIENTS: WATER; AMMONIUM LAURYL SULFATE; COCAMIDOPROPYL BETAINE; COCO MONOETHANOLAMIDE; GLYCOL DISTEARATE; DIMETHICONE; TRIDECETH-5; SODIUM CHLORIDE; PANTHENOL; CETOSTEARYL ALCOHOL; ALLANTOIN; EDETATE DISODIUM; CITRIC ACID MONOHYDRATE; METHYLCHLOROISOTHIAZOLINONE; METHYLISOTHIAZOLINONE

Panrosa FRESH CLEAN Pyrithione Zinc Dandruff Shampoo

Active ingredient

Pyrithione zinc 1%

Purpose

Antidandruff

Use

helps prevent recurrence of flaking and itching
associated with dandruff.

Warnings

For external use only

When using this product

avoid contact with eyes. If contact occurs, rinse eyes thoroughly with water.

Stop use and ask a doctor if

condition worsens or does not improve after regular use of this product as directed.

Keep out of reach of children.

If swallowed, get medical help or contact Poison Control Center right away.

Directions

- Shake well
- Wet hair
- Massage shampoo into scalp
- Rinse
- Repeat if desired
- For best results, use at least twice a week or as directed by a doctor
- For maximum dandruff control, use every time you shampoo

Inactive ingredients

Water, Sodium Larueth Sulfate, Ammonium Lauryl Sulfate, Cocamidopropyl Betaine, Cocamide MEA, Glycol Distearate, Dimethicone, Trideceth-5, Sodium Dodecylbenzenesulfonate, Sodium Chloride, Panthenol, Hydroxypropyl Guar, Cetearyl Alcohol, Fragrance, Allantoin, Disodium EDTA, Citric Acid, Methylchloroisothiazolinone, Methylisothiazolinone.

Panrosa FRESH CLEAN Pyrithione Zinc Dandruff Shampoo 443.66ml (50320-400-43)

PANROSA
FRESH CLEAN
BASIC HAIR CARE
Pyrithione Zinc Dandruff Shampoo
Deep cleaning for soothing relief of itchy, flaky scalp
15 fl oz (443.6 mL)
Distributed by:
Panrosa
ENTERPRISES, INC.
1969 S. Campus Ave.
Ontario, California 91761 U.S.A.
Made in China
Questions please visit our web site at www.panrosa.com
Package is recyclable where facilities exist.